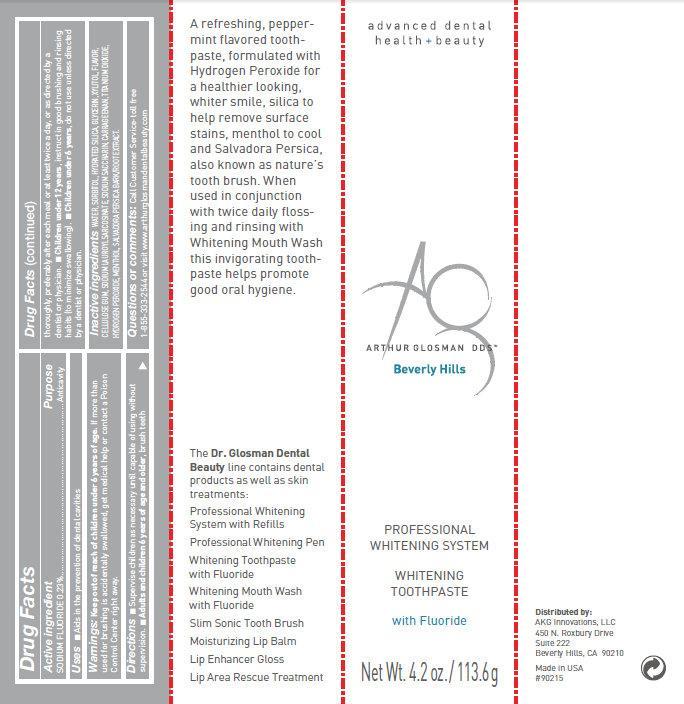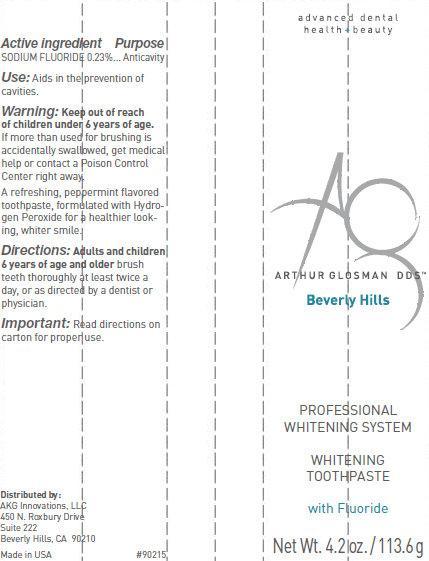 DRUG LABEL: PROFESSIONAL WHITENING SYSTEM WHITENING
NDC: 62111-0213 | Form: PASTE
Manufacturer: AKG Innovations LLC
Category: otc | Type: HUMAN OTC DRUG LABEL
Date: 20140214

ACTIVE INGREDIENTS: SODIUM FLUORIDE 0.23 g/100 g
INACTIVE INGREDIENTS: WATER; SORBITOL; HYDRATED SILICA; GLYCERIN; XYLITOL; CARBOXYMETHYLCELLULOSE SODIUM; SODIUM LAUROYL SARCOSINATE; SODIUM SARCOSINATE; CARRAGEENAN; TITANIUM DIOXIDE; HYDROGEN PEROXIDE; MENTHOL; SALVADORA PERSICA ROOT

PROFESSIONAL WHITENING SYSTEM WHITENING TOOTHPASTE with Fluoride

PROFESSIONALWHITENING SYSTEM WHITENINGTOOTHPASTE with Fluoride

Active Ingredient

SODIUM FLUORIDE 0.23%...

Purpose

Anticavity

Uses

Aids in the prevention of dental cavities.

Warnings

Keep out of reach of children under 6 years of age. If more than used for brushing is accidentally swallowed, get medical help or contact a Poison Control Center right away.

Directions

Supervise children as necessary until capable of using without supervision.

■ Adults and children 6 years of age and older, brush teeth thoroughly, preferably after each meal or at least twice a day, or as directed by a

dentist or physician.

■ Children under 12 years, instruct in good brushing and rinsing habits (to minimize swallowing).

■ Children under 6 years, do not use unless directed by a dentist or physician.

Inactive Ingredients

WATER, SORBITOL, HYDRATED SILICA, GLYCERIN, XYLITOL, FLAVOR,

CELLULOSE GUM, SODIUM LAUROYL SARCOSINATE, SODIUM SACCHARIN, CARRAGEENAN, TITANIUM DIOXIDE,

HYDROGEN PEROXIDE, MENTHOL, SALVADORA PERSICA BARK/ROOT EXTRACT.

Questions or comments:

Call Customer Service-toll free

1-855-333-2544 or visit www.arthurglosmandentalbeauty.com

PROFESSIONALWHITENING SYSTEM WHITENINGTOOTHPASTE with Fluoride 113.6 g (62111-0213-2)

advanced dental

health +beauty

ARTHUR GLOSMAN DDS

Beverly Hills

PROFESSIONAL

WHITENING SYSTEM

WHITENING

TOOTHPASTE

with Fluoride

Net Wt. 4.2 oz. / 113.6 g

A refreshing, peppermint flavored toothpaste, formulated with Hydrogen Peroxide for a healthier looking, whiter smile, silica tohelp remove surface stains, menthol to cool and Salvadora Persica, also known as nature’s tooth brush. When used in conjunctionwith twice daily flossing and rinsing with Whitening Mouth Wash this invigorating toothpaste helps promote good oral hygiene.

The Dr. Glosman Dental Beauty line contains dental products as well as skin treatments:

Professional Whitening System with Refills

Professional Whitening Pen

Whitening Toothpaste with Fluoride

Whitening Mouth Wash with Fluoride

Slim Sonic Tooth Brush

Moisturizing Lip Balm

Lip Enhancer Gloss

Lip Area Rescue Treatment

Important:

Read directions on

carton for proper use.

Distributed by:

AKG Innovations, LLC

450 N. Roxbury Drive

Suite 222

Beverly Hills, CA 90210

Made in USA #90215